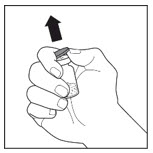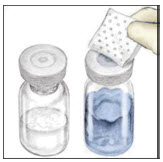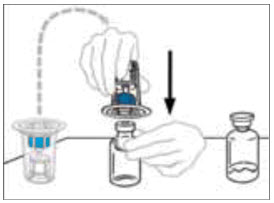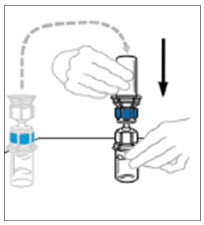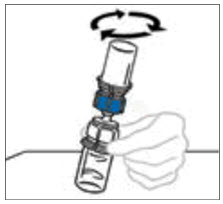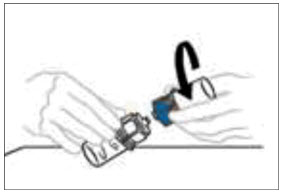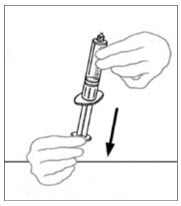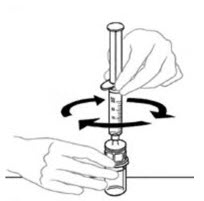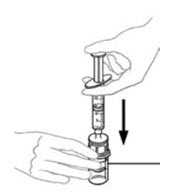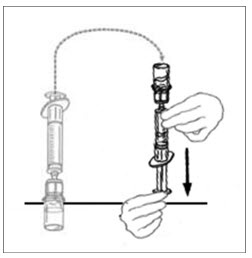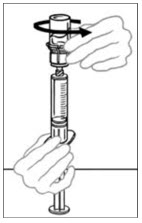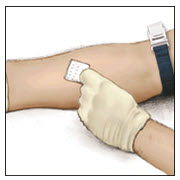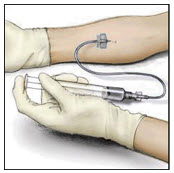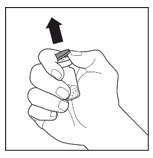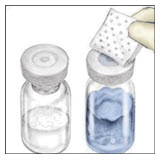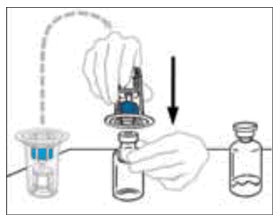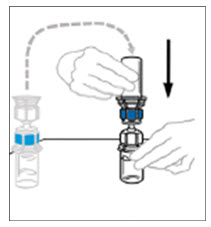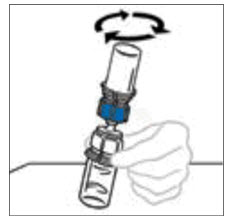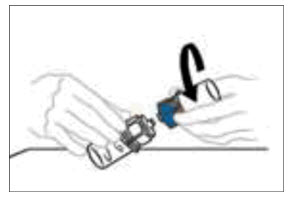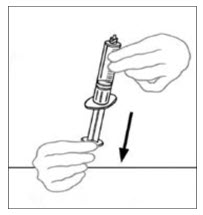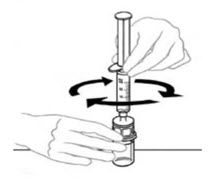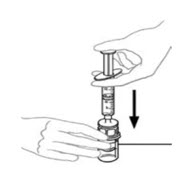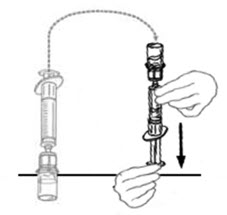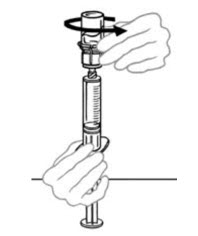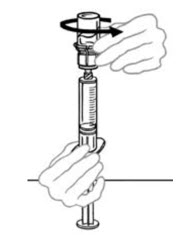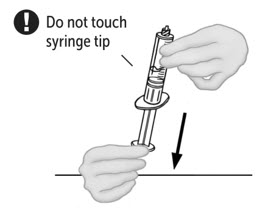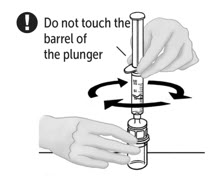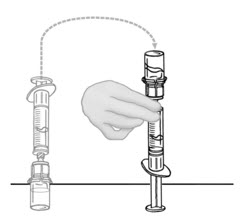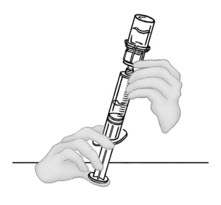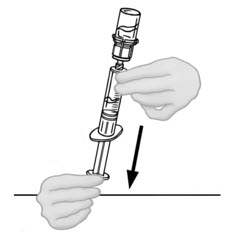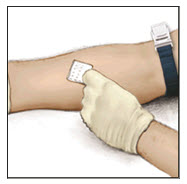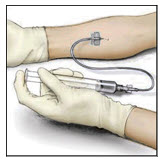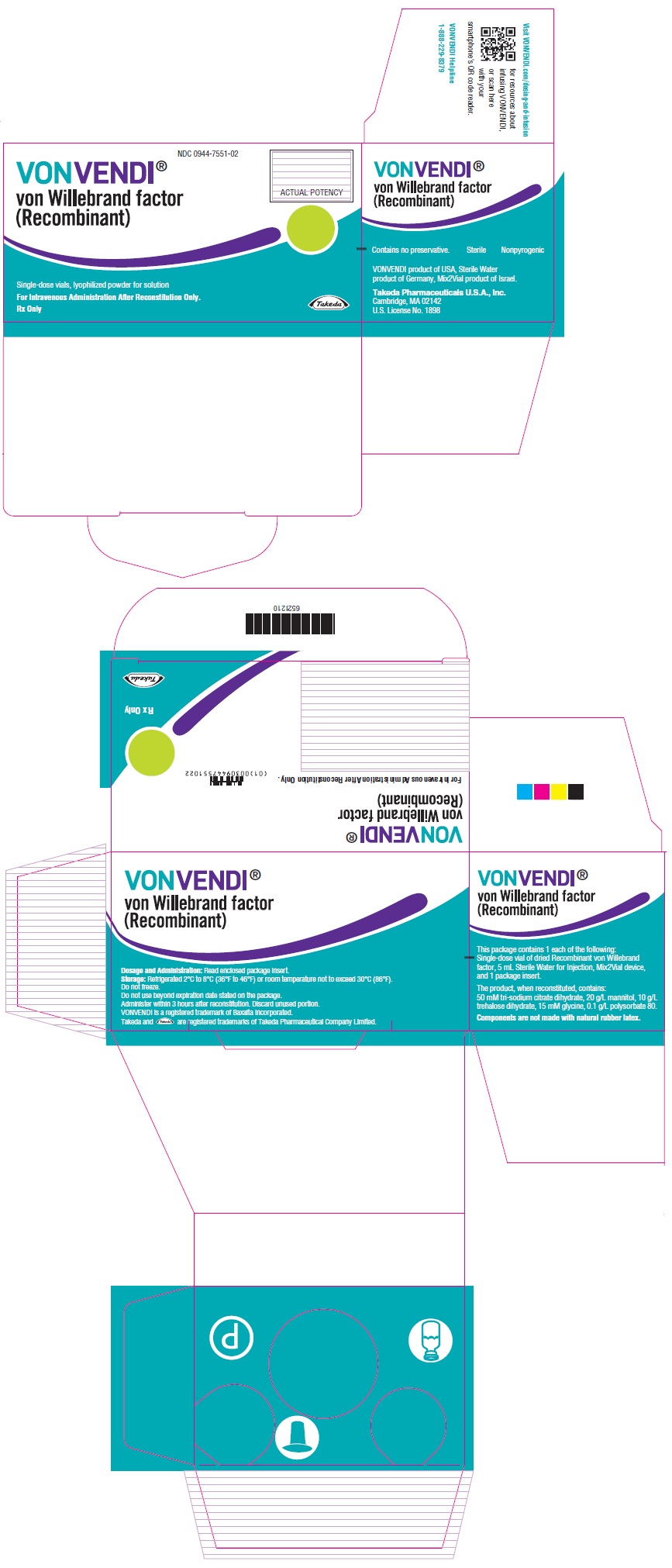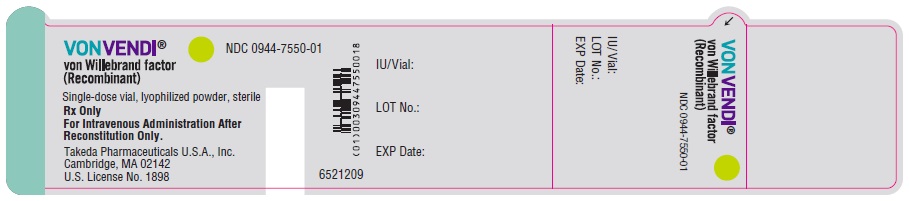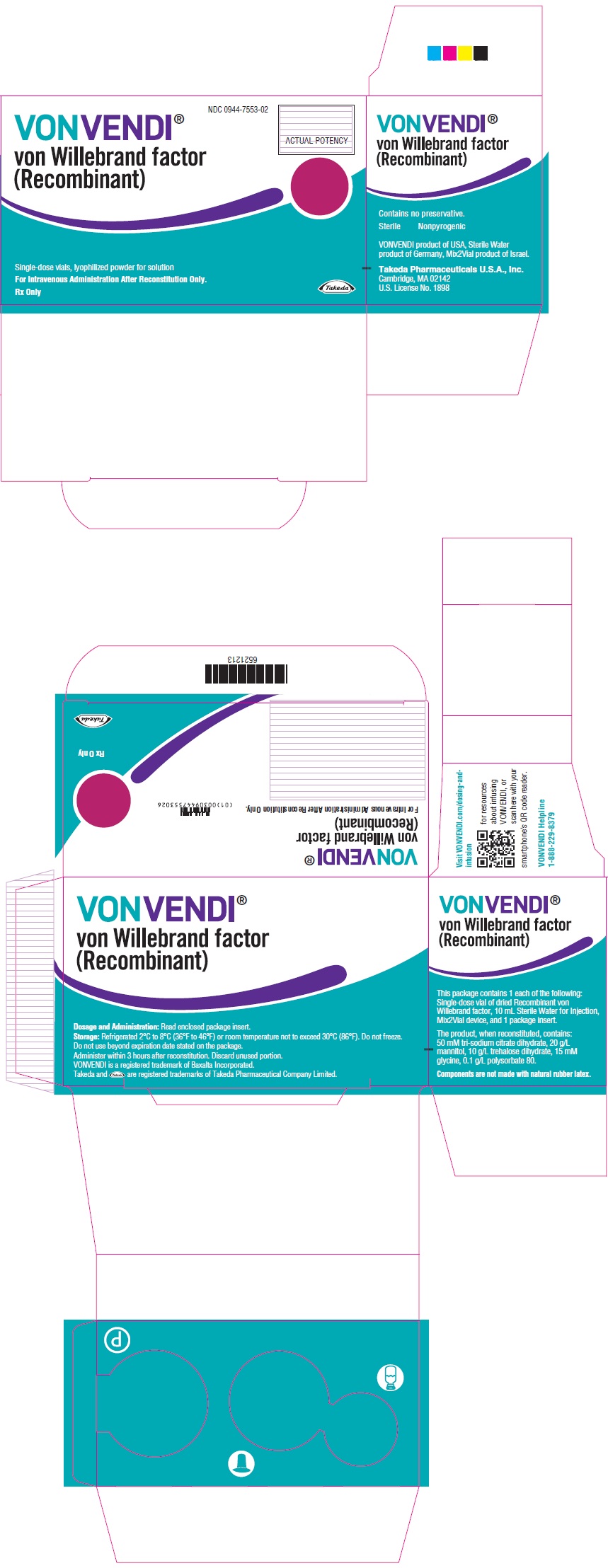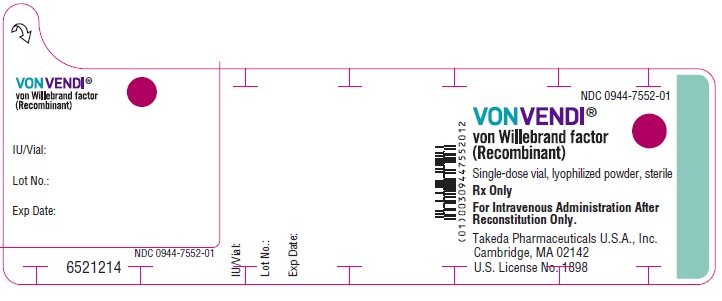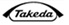 DRUG LABEL: VONVENDI
NDC: 0944-7551 | Form: KIT | Route: INTRAVENOUS
Manufacturer: Takeda Pharmaceuticals America, Inc.
Category: other | Type: PLASMA DERIVATIVE
Date: 20251024

ACTIVE INGREDIENTS: VON WILLEBRAND FACTOR HUMAN 650 [iU]/5 mL
INACTIVE INGREDIENTS: TRISODIUM CITRATE DIHYDRATE; GLYCINE; MANNITOL; TREHALOSE DIHYDRATE; POLYSORBATE 80; WATER 5 mL/5 mL

HIGHLIGHTS OF PRESCRIBING INFORMATION

These highlights do not include all the information needed to use VONVENDI® safely and effectively. See full prescribing information for VONVENDI.
VONVENDI [von Willebrand factor (recombinant)] lyophilized powder for solution, for intravenous injection
Initial U.S. Approval: 2015

RECENT MAJOR CHANGES

Indications and Usage (1) | 9/2025
Dosage and Administration (2.1, 2.2) | 9/2025
Warnings and Precautions (5.1, 5.2, 5.3) | 9/2025

1 INDICATIONS AND USAGE

VONVENDI [von Willebrand factor (recombinant)] is a recombinant von Willebrand factor (rVWF) indicated in adult and pediatric patients with von Willebrand disease (VWD) for:

- On-demand treatment and control of bleeding episodes. (1)
- Perioperative management of bleeding. (1)

For adult patients only:

- Routine prophylaxis to reduce the frequency of bleeding episodes. (1)

2 DOSAGE AND ADMINISTRATION

For intravenous use after reconstitution only.

On-Demand Treatment and Control of Bleeding Episodes

- For each bleeding episode, administer the first dose of VONVENDI with an approved recombinant (non-von Willebrand factor containing) factor VIII, if factor VIII baseline levels are below 40% or are unknown. (2.2)
- Initial dose is 40 to 80 International Units (IU) per kg body weight (BW). Adjust the dosage based on the extent and location of bleeding. (2.2)

Bleeding Episode | Initial Dose | Subsequent Dose
Minor | 40 to 50 IU/kg | 40 to 50 IU/kg every 8 to 24 hours
Major | 50 to 80 IU/kg | 40 to 60 IU/kg every 8 to 24 hours for approximately 2 to 3 days

Perioperative Management of Bleeding

For Elective Surgical Procedure

- A dose of VONVENDI may be given 12 to 24 hours prior to surgery to allow the endogenous factor VIII levels to increase to at least 30 IU/dL (minor surgery) or 60 IU/dL (major surgery). (2.2)
- Assess FVIII:C levels within 3 hours prior to surgery. If the FVIII:C levels are at or above the recommended minimum target levels, administer a dose of VONVENDI alone within 1 hour prior to the procedure. If the FVIII:C levels are below the recommended minimum target levels, administer recombinant factor VIII in addition to VONVENDI to raise VWF:RCo and FVIII:C. (2.2)

For Emergency Surgery

- Assess baseline VWF:RCo and FVIII:C levels within 3 hours prior to surgery. If not available, use weight-based dosing calculation. (2.2)
- Administer VONVENDI 1 hour before surgery with or without recombinant factor VIII and adjust the dose to raise VWF:RCo and FVIII:C to adequate level. (2.2)

Type of Surgery | VWF:RCo Target Peak Plasma Level | FVIII:C Target Peak Plasma Level | Calculation of rVWF Dose (IU VWF:RCo required)
Minor | 50 to 60 IU/dL | 40 to 50 IU/dL | ∆ VWF:RCo x BW (kg)/IR
Major | 100 IU/dL | 80 to 100 IU/dL | ∆ VWF:RCo x BW (kg)/IR

- Continue to monitor the VWF:RCo and FVIII:C plasma levels after surgical procedure. (2.2)

Routine Prophylaxis in Adults

Initial dosage of VONVENDI is 40 to 60 IU/kg body weight to be administered twice weekly. Treat breakthrough bleeding as per dosing guidelines. (2.2)

3 DOSAGE FORMS AND STRENGTHS

VONVENDI is available as a lyophilized powder in single-dose vials containing nominally 650 or 1300 international units VWF:RCo. (3)

4 CONTRAINDICATIONS

Do not use in patients who have had life-threatening hypersensitivity reactions to VONVENDI or its components (tri-sodium citrate-dihydrate, glycine, mannitol, trehalose-dihydrate polysorbate 80, and hamster or mouse proteins). (4)

5 WARNINGS AND PRECAUTIONS

- Thromboembolic events have occurred with VONVENDI. Patients with known risk factors for thrombosis are at higher risk. Monitor for early signs of thrombosis and have prophylaxis measures against thromboembolism instituted according to current recommendations. In patients requiring frequent doses of VONVENDI in combination with recombinant factor VIII, monitor plasma levels for FVIII:C because sustained excessive factor VIII plasma levels can increase the risk for thromboembolic events. (5.1)
- Hypersensitivity and infusion-related reactions, including anaphylaxis, may occur. Discontinue VONVENDI if hypersensitivity symptoms occur and administer appropriate emergency treatment. (5.2)
- Neutralizing antibodies to von Willebrand factor (VWF) and/or factor VIII can occur with VONVENDI. If the expected plasma levels of VWF activity (VWF:RCo) are not attained, or if bleeding is not controlled with an appropriate dose, perform an appropriate assay to determine if an anti-VWF or anti-factor VIII inhibitors are present. (5.3)

6 ADVERSE REACTIONS

The most common adverse reactions observed (≥2% of patients) were headache, vomiting, nausea, dizziness and generalized pruritus. (6.1)

To report SUSPECTED ADVERSE REACTIONS, contact Takeda Pharmaceuticals U.S.A., Inc. at 1-877-TAKEDA-7 (1-877-825-3327) or FDA at 1-800-FDA-1088 or www.fda.gov/medwatch.

FULL PRESCRIBING INFORMATION

1 INDICATIONS AND USAGE

VONVENDI® is indicated in adult and pediatric patients with von Willebrand disease (VWD) for:

- On-demand treatment and control of bleeding episodes.
- Perioperative management of bleeding.

For adult patients only:

- Routine prophylaxis to reduce the frequency of bleeding episodes.,

2 DOSAGE AND ADMINISTRATION

2.1 Important Dosing Information

For intravenous use after reconstitution only.

- Each vial of VONVENDI is labeled with the actual amount of rVWF activity in International Units (IU), as measured with the Ristocetin cofactor assay (VWF:RCo).
- Individualize dosage and frequency according to the patient’s weight, type, location, and severity of the bleeding episodes/surgical intervention and monitoring of appropriate clinical and laboratory measures [see Warnings and Precautions (5.2, 5.3)].
- If the patient's baseline plasma FVIII:C level is below 40%, or is unknown, administer an approved recombinant (non-von Willebrand factor containing) factor VIII (rFVIII) with the first infusion of VONVENDI to achieve a hemostatic plasma level of FVIII:C.
- If an immediate rise in FVIII:C is not necessary, administer VONVENDI without rFVIII. Depending on the patient’s baseline FVIII:C level, a single infusion of VONVENDI is expected to increase endogenous FVIII:C activity above 40% within 6 hours.
- See rFVIII package insert for reconstitution and administration instructions.
- When repeated infusions are required, monitor factor VIII levels to determine if rFVIII is required with subsequent infusions.

2.2 Recommended Dosage

On-Demand Treatment and Control of Bleeding Episodes

- The recommended dose of VONVENDI is based on the type of bleeding episodes. Dosing guidelines for treatment of minor and major bleeds in adult and pediatric patients are provided in Table 1.

Table 1: Dosing Guidelines for Bleeding Episodes
Bleeding Episodes | Initial Dose | Subsequent Dose (as clinically required)
Minor (e.g., readily managed epistaxis, oral bleeding, menorrhagia) | 40 to 50 IU/kg | 40 to 50 IU/kg every 8 to 24 hours
Major [A bleed could be considered major if red blood cell transfusion is either required or potentially indicated or if bleeding occurs in a critical anatomical site (e.g., intracranial or gastrointestinal hemorrhage).] (e.g., severe or refractory epistaxis, menorrhagia, GI bleeding, CNS trauma, hemarthrosis, or traumatic hemorrhage) | 50 to 80 IU/kg | 40 to 60 IU/kg every 8 to 24 hours for approximately 2 to 3 days

- The initial dose of VONVENDI should achieve greater than 60% of von Willebrand factor (VWF) levels (based on VWF:RCo greater than 60 IU/dL) and an infusion of rFVIII should achieve factor VIII levels greater than 40% (FVIII:C greater than 40 IU/dL). In major bleeding episodes, maintain trough levels of VWF:RCo greater than 50% for as long as deemed necessary.
- Administer VONVENDI with rFVIII if the FVIII:C level is less than 40%, or is unknown, to control bleeding. The rFVIII dose should be calculated according to the difference between the patient’s baseline plasma FVIII:C level, and the desired peak FVIII:C level to achieve an appropriate plasma FVIII:C level based on the approximate mean recovery of 2 (IU/dL)/(IU/kg).
- Administer the complete dose of VONVENDI followed by rFVIII within 10 minutes.

Calculating Dose

VONVENDI dose [IU] = dose in [IU/kg] x body weight [kg]

In a major bleeding episode when baseline factor VIII level is unknown, rFVIII should be administered to achieve a target peak level of FVIII:C 80 to100 IU/dL, based on the approximate mean recovery of 2 (IU/dL)/(IU/kg). Refer to label for weight-based dose calculation of rFVIII that is used.

If expected VWF activity plasma levels are not attained, or if bleeding episode is not controlled with an appropriate dose, perform an assay that measures the presence of VWF or factor VIII inhibitors [see Warnings and Precautions (5.3)].

Perioperative Management of Bleeding

Elective Surgical Procedures

- A preoperative dose of VONVENDI may be administered 12 to 24 hours prior to surgery to allow the endogenous factor VIII levels to increase to at least 30 IU/dL (minor surgery) or 60 IU/dL (major surgery) before the loading dose (1 hour preoperative dose) of VONVENDI with or without rFVIII. Ensure baseline FVIII:C level is available prior to determining the need for 12 to 24 hour preoperative dose.
- FVIII:C level should also be assessed within 3 hours prior to initiating the surgical procedure. If the level is at the recommended minimum target levels (30 IU/dL for minor surgery and 60 IU/dL for major surgery), administer a dose of VONVENDI alone (without factor VIII treatment) within 1 hour prior to the procedure. If the FVIII:C level is below the recommended minimum target level, administer complete dose of VONVENDI followed by rFVIII within 10 minutes to raise VWF:RCo and FVIII:C.
- Refer to Table 2 for recommended VWF:RCo and FVIII:C target peak plasma levels and dosing guidelines for perioperative management of bleeding in adult and pediatric patients. When possible, measure incremental recovery (IR) for VONVENDI before surgery. For calculation of IR, measure baseline plasma VWF:RCo. Then infuse a dose of 50 IU/kg of VONVENDI. Measure VWF:RCo, 30 minutes after infusion of VONVENDI.

Use the following formula to calculate IR:

IR = [Plasma VWF:RCo at 30 minutes (IU/dL) – Plasma VWF:RCo at baseline (IU/dL)]/Dose (IU/kg)

Emergency Surgery

- A 12 to 24 hour preoperative dose may not be feasible in patients requiring emergency surgery. Baseline VWF:RCo and FVIII:C levels should be assessed within 3 hours prior to initiating the surgical procedure if it is feasible. If baseline VWF:RCo and FVIII:C are available, the loading dose (1 hour preoperative dose) can be calculated as the difference in the target peak and baseline plasma VWF:RCo levels divided by the IR. If the IR is not available, assume an IR of 2.0 IU/dL per IU/kg.
- If baseline VWF:RCo and FVIII:C are not available, as a general guidance a loading dose (1 hour preoperative dose) of VONVENDI, 40 to 60 IU/kg VWF:RCo, should be administered. Additionally, rFVIII at a dose of 30 to 45 IU/kg may be infused sequentially, preferably within 10 minutes after the VONVENDI infusion in patients whose factor VIII plasma levels already are (or are highly likely to be) less than 40 to 50 IU/dL for minor surgery or 80 to 100 IU/dL for major surgery.

Refer to Table 2 for recommended VWF:RCo and FVIII:C target peak plasma levels and dosing guidelines for perioperative management of bleeding.

Table 2: Recommended VWF:RCo and FVIII:C Target Peak Plasma Levels for the Perioperative Management of Bleeding
Type of Surgery | VWF:RCo Target Peak Plasma Level | FVIII:C Target Peak Plasma Level [Additional recombinant factor VIII may be required to attain the recommended FVIII:C target peak plasma levels. Dosing guidance should be done based on the IR. If the IR is not available, assume an IR of 2.0 IU/dL per IU/kg. Calculation of factor VIII dose: Target FVIII:C - Baseline FVIII:C/IR] | Calculation of rVWF Dose (to be administered within 1 hour prior to surgery) (IU VWF:RCo required)
Minor | 50 to 60 IU/dL | 40 to 50 IU/dL | ∆ [∆ = Target peak plasma VWF:RCo – **baseline plasma VWF:RCo] VWF:RCo x BW (kg) /IR [IR = Incremental Recovery as measured in the patient. If the IR is not available, assume an IR of 2.0 IU/dL per IU/kg. ** Baseline plasma VWF:RCo is VWF:RCo activity level assessed within 3 hours prior to administration of 12 to 24 hours preoperative dose of VONVENDI. If no dose is administered 12 to 24 hours preoperatively, it’s recommended to use the VWF:RCo levels prior to surgery.]
Major | 100 IU/dL | 80 to 100 IU/dL | ∆ VWF:RCo x BW (kg) /IR

In the absence of available baseline FVIII:C, VWF:RCo and IR, it is recommended to use body weight-based dosing as outlined below in Table 3.

Table 3: Recommended Body Weight (BW) Based Dosing for the Perioperative Management of Bleeding
Type of Surgery | VWF:RCo (IU VWF:RCo/kg BW) | VWF:RCo Target Peak Plasma Level | FVIII:C (IU FVIII:C/ kg BW) | FVIII:C Target Peak Plasma Level
Minor | 25 to 30 IU/kg | 50 to 60 IU/dL | 20 to 25 IU/kg | 40 to 50 IU/dL
Major | 50 ± 10 IU/kg | 100 IU/dL | 40 to 50 IU/kg | 80 to 100 IU/dL

- Monitor VWF:RCo and FVIII:C plasma levels starting 12 to 24 hours after surgery and at least every 24 hours in the perioperative period to adjust the dosing of VONVENDI or rFVIII levels. VWF:RCo and FVIII:C plasma levels should be monitored and the intra- and postoperative maintenance regimen should be individualized according to the pharmacokinetic (PK) results and intensity and duration of the hemostatic challenge.
- Refer to Table 4 for recommended VWF:RCo and FVIII:C target trough plasma levels and minimum duration of treatment for subsequent maintenance doses after surgery.

Table 4: Recommended VWF:RCo and FVIII:C Target Trough Plasma Levels and Minimum Duration of Treatment for Subsequent Maintenance Doses
Type of Surgery | VWF:RCo Target Trough Plasma Level up to 72 Hours Post-Surgery | VWF:RCo Target Trough Plasma Level after 72 Hours Post-Surgery | FVIII:C Target Trough Plasma Level up to 72 Hours Post-Surgery | FVIII:C Target Trough Plasma Level after 72 Hours Post-Surgery | Minimum Duration of Treatment | Frequency of Dosing
Minor | ≥30 IU/dL | - | >30 IU/dL | - | 48 hours | Every 12 to 24 hours to every other day
Major | >50 IU/dL | >30 IU/dL | >50 IU/dL | >30 IU/dL | 72 hours | Every 12 to 24 hours to every other day

Routine Prophylaxis in Adults

For initiation of prophylactic treatment, administer 40 to 60 IU of VONVENDI per kg of body weight twice weekly. Treat breakthrough bleeding as per the dosing guidelines in Table 1.

2.3 Preparation and Reconstitution

- Allow VONVENDI and Sterile Water for Injection (diluent) to reach room temperature.
- If the patient requires more than one vial of VONVENDI per injection, reconstitute each vial according to the following instructions.
- Some flakes or particles may remain in the reconstituted vial. The filter included in the Mix2Vial device will remove extraneous flakes or particles, and the resulting solution in the syringe should be clear and colorless. Do not use the solution in the syringe if it is cloudy or contains flakes or particles after filtration from the vial into the syringe.

Reconstitution

1. Remove the plastic caps from the VONVENDI and water for injection vials.

2. Clean the rubber stoppers with a sterile alcohol swab.

3. Peel back the cover of the Mix2Vial transfer device. To maintain sterility, leave the Mix2Vial device in the clear plastic packaging.
4. While firmly holding the diluent vial on a level surface, take the Mix2Vial in its plastic package and invert it over the diluent vial. Push the blue plastic cannula of the Mix2Vial firmly straight down through the rubber stopper. Carefully remove the plastic package leaving the Mix2Vial attached firmly to the diluent vial.

5. Hold the VONVENDI vial firmly on a level surface, quickly invert the diluent vial with the Mix2Vial attached and push the transparent plastic cannula end of the Mix2Vial firmly straight down through the stopper of the VONVENDI vial. The diluent will be drawn into the VONVENDI vial by the vacuum.

6. Verify that diluent transfer is complete. Do not use if vacuum has been lost.
7. With both vials still attached, gently swirl the vials or allow the reconstituted product to sit for 5 minutes then gently swirl to ensure the powder is completely dissolved.
  Do not shake. Shaking will adversely affect the integrity of the product.
  Note: Some flakes or particles may remain in the reconstituted vial. The filter included in the Mix2Vial device will remove extraneous flakes or particles, and the resulting solution in the syringe should be clear and colorless. Do not use the solution in the syringe if it is cloudy or contains flakes or particles after filtration from the vial into the syringe.

8. Once the content is completely dissolved, firmly hold both the transparent and blue parts of the Mix2Vial. Unscrew the Mix2Vial into two separate pieces and discard the empty diluent vial and the blue part of the Mix2Vial. Note: The Mix2Vial is intended for one-time use with a single vial of VONVENDI and diluent only. If the dose requires more than one vial of VONVENDI, reconstitute each vial separately.
  Do not refrigerate after reconstitution.

2.4 Administration

For intravenous administration only.

- Administer VONVENDI immediately after reconstitution. If not, store at room temperature not to exceed 25°C (77°F) for up to 3 hours. Discard after 3 hours.
- No more than two vials of VONVENDI may be pooled into a single syringe. Pooling of more than two vials into a syringe may result in formation of filaments, which requires discarding of the solution in the syringe. If a patient is to receive more than one vial of VONVENDI, leave syringe attached to the vial or cover syringe tip with a suitable sterile cap until ready to infuse to reduce risk of contamination.
- Use plastic syringes with this product because proteins in the product tend to stick to the surface of glass syringes.
- Do not mix VONVENDI with other medicinal products.

Administration

1. Draw air into an empty, sterile disposable plastic syringe. The amount of air should equal the amount of reconstituted VONVENDI to be withdrawn from the vial.

2. Leaving the VONVENDI vial (containing the dissolved product) on your flat work surface, connect the syringe to the clear plastic connector by attaching and turning the syringe clockwise (Figure A). Hold the vial with one hand and use the other hand to push the entire amount of air from the syringe into the vial (Figure B). The required amount of product will not be drawn into the syringe if all the air is not pushed into the vial.

Figure A

Figure B

3. Flip connected syringe and VONVENDI vial so the vial is on top. Be sure to keep the syringe plunger pressed in. Draw the VONVENDI into the syringe by pulling plunger back slowly. Do not push and pull solution back and forth between syringe and vial. Doing so may harm the integrity of the product.

4. Inspect VONVENDI after filtration/withdrawal into the syringe for discoloration and particulate matter prior to administration. The solution should be clear or slightly opalescent in appearance. Do not administer if particulate matter, discoloration, or cloudiness is observed and notify Takeda Medical Information 1-877-TAKEDA-7 (1-877-825-3327).
5. When ready to infuse, firmly hold the barrel of the syringe (keeping the syringe plunger facing down) and detach the Mix2Vial from the syringe. Discard the Mix2Vial (transparent plastic part) and the empty VONVENDI vial. If a patient is to receive more than one vial of VONVENDI, the contents of up to two vials may be drawn into a single syringe. When pushing air into a second vial of VONVENDI to be pooled into a syringe, position the vial and connected syringe so that the vial is on top.

6. Clean the intended injection site with a sterile alcohol swab.

7. Attach a suitable infusion needle to the syringe. Infuse intravenously at a rate slow enough that ensures the comfort of the patient, up to a maximum of 4 mL per minute.

8. If tachycardia occurs, the injection speed must be reduced or the administration must be interrupted.
9. Dispose of any unused product or waste material in accordance with local requirements.

3 DOSAGE FORMS AND STRENGTHS

VONVENDI is available as a non-pyrogenic, white to off-white, lyophilized powder for reconstitution in single-dose vials containing nominally 650 or 1300 IU VWF:RCo/vial.

Each VONVENDI vial is labeled with the number of units of VWF:RCo expressed in IU, which are based on the current World Health Organization (WHO) standard for VWF concentrate.

4 CONTRAINDICATIONS

VONVENDI is contraindicated in patients who have had life-threatening hypersensitivity reactions to VONVENDI or constituents of the product (tri-sodium citrate-dihydrate, glycine, mannitol, trehalose-dihydrate, polysorbate 80, and hamster or mouse proteins) [see Warning and Precautions (5.2) and Description (11)].

5 WARNINGS AND PRECAUTIONS

5.1 Thromboembolic Events

Thromboembolic events have occurred with VONVENDI [see Adverse Reactions (6.1)]. These events can include disseminated intravascular coagulation (DIC), venous thrombosis, pulmonary embolism, myocardial infarction, and stroke. Patients with known risk factors for thrombosis, including low ADAMTS13 levels, are at a higher risk [see Description (11)]. Monitor patients for signs and symptoms of thrombosis such as pain, swelling, discoloration, dyspnea, cough, hemoptysis, and syncope. Institute prophylaxis measures against thromboembolism according to current clinical practice and standard of care.

In patients requiring frequent doses of VONVENDI in combination with rFVIII, monitor plasma levels for FVIII:C activity because sustained excessive factor VIII plasma levels can increase the risk of thromboembolic complications.

5.2 Hypersensitivity and Infusion-Related Reactions

Hypersensitivity reactions and infusion-related reactions have occurred with VONVENDI [see Adverse Reactions (6.1). These reactions can include anaphylactic shock, generalized urticaria, angioedema, chest tightness, hypotension, shock, lethargy, nausea, vomiting, paresthesia, pruritus, restlessness, blurred vision, wheezing and/or acute respiratory distress. If signs and symptoms of severe allergic reactions occur, immediately discontinue administration of VONVENDI and provide appropriate supportive care.

VONVENDI contains trace amounts of mouse immunoglobulin G (MuIgG) and hamster proteins less than or equal to 2 ng/IU VONVENDI. Patients treated with this product may develop hypersensitivity reactions to non-human mammalian proteins.

5.3 Neutralizing Antibodies

Neutralizing antibodies to VWF and/or factor VIII can occur with VONVENDI. If the expected plasma levels of VWF activity (VWF:RCo) are not attained, perform an appropriate assay to determine if anti-VWF or anti-factor VIII inhibitors are present. Consider other therapeutic options and direct the patient to a physician with experience in the care of either VWD or hemophilia A.

In patients with high levels of inhibitors to VWF or factor VIII, VONVENDI therapy may not be effective, and infusion of this protein may lead to severe hypersensitivity reactions. Since inhibitor antibodies can occur concomitantly with anaphylactic reactions, evaluate patients experiencing an anaphylactic reaction for the presence of inhibitors.

5.4 Monitoring Laboratory Tests

Monitor plasma levels of VWF:RCo and factor VIII activities in patients receiving VONVENDI to avoid sustained excessive VWF and/or factor VIII activity levels, which may increase the risk of thrombotic events, particularly in patients with known clinical or laboratory risk factors.

Monitor for development of VWF and/or factor VIII inhibitors when suspected. Perform appropriate inhibitor assays to determine if VWF and/or factor VIII inhibitors are present if bleeding is not controlled with the expected dose of VONVENDI.

6 ADVERSE REACTIONS

6.1 Clinical Trials Experience

Because clinical trials are conducted under widely varying conditions, adverse reaction rates observed in the clinical trials of a drug cannot be directly compared to rates in clinical trials of another drug and may not reflect the rates observed in clinical practice.

The safety data described in this section reflects exposure of VONVENDI in six clinical studies (Study 1, Study 2, Study 3, Study 4, Study 5 and Study 6) in patients with von Willebrand Disease (VWD). A total of 103 adult and 29 pediatric patients received intravenous infusion of VONVENDI with or without rFVIII with a median dose of 311 IU/kg per patient (range of 2 to 29593 IU/kg). The patients were followed for up to 4.6 years.

The most common adverse reactions observed in greater than or equal to 2% of patients in clinical trials with VONVENDI (n=132) were headache, vomiting, nausea, dizziness and generalized pruritus.

Table 5 lists the adverse reactions reported with VONVENDI from pooled safety population from six clinical studies.

Table 5: Adverse Reactions
System Organ Class (SOC) | Adverse Reaction | Total (N=132) n (%)
Cardiac Disorders | Tachycardia | 1 (0.8%)
Gastrointestinal Disorders | Vomiting | 9 (7%)
- | Nausea | 7 (5%)
General Disorders and Administration Site Conditions | Infusion site paresthesia | 1 (0.8%)
- | Infusion-related reaction [One patient developed infusion-related reaction experiencing chest discomfort and increased heart rate.] | 1 (0.8%)
Skin and Subcutaneous Tissues Disorders | Generalized pruritus | 3 (2%)
Vascular Disorders | Hypertension | 2 (2%)
- | Hot flush | 1 (0.8%)
- | Deep vein thrombosis | 1 (0.8%)
Nervous System Disorders | Headache | 18 (14%)
- | Dizziness | 4 (3%)
- | Vertigo | 2 (2%)
- | Dysgeusia | 1 (0.8%)
- | Tremor | 1 (0.8%)
Investigations | Electrocardiogram T wave inversions | 1 (0.8%)

6.2 Postmarketing Experience

The following adverse reactions have been identified during post-approval use of VONVENDI. Because these reactions are reported voluntarily from a population of uncertain size, it is not always possible to reliably estimate their frequency or establish a causal relationship to drug exposure.

Immune System Disorders: Hypersensitivity including anaphylactic reaction; Infusion related reaction.

8 USE IN SPECIFIC POPULATIONS

8.1 Pregnancy

Risk Summary

Adequate and well-controlled studies with VONVENDI have not been conducted in pregnant women. Animal developmental and reproductive toxicity studies have not been conducted with VONVENDI. It is not known whether VONVENDI can cause fetal harm when administered to a pregnant woman or whether it can affect reproduction capacity.

The background risk of major birth defects and miscarriage in the indicated population is unknown; however, in the US population, the estimated background risk of major birth defects and miscarriage is 2 to 4% and 15 to 20%, respectively.

8.2 Lactation

Risk Summary

There is no information regarding the presence of VONVENDI in human milk, the effects on the breastfed infant, or the effects on milk production.

The developmental and health benefits of breastfeeding should be considered along with the mother’s clinical need for VONVENDI and any potential adverse effects on the breastfed infant from VONVENDI or from the underlying maternal condition.

8.4 Pediatric Use

The safety and effectiveness of VONVENDI for on-demand treatment of bleeding episodes and perioperative management of bleeding have been established in pediatric patients. The use of VONVENDI was supported by evidence from Study 3 and Study 6 which included 26 pediatric patients 1 to 16 years of age [see Adverse Reactions (6.1) and Clinical Studies (14)].

8.5 Geriatric Use

Clinical studies with VONVENDI included 4 (3%) patients aged 65 years and above. No overall differences in safety or effectiveness were observed between these and younger patients.

11 DESCRIPTION

VONVENDI is a purified rVWF expressed in Chinese Hamster Ovary (CHO) cells. VONVENDI is produced and formulated without the addition of any exogenous raw materials of human or animal origin in the cell culture, purification, or formulation of the final product. Proteins present in the final container product other than rVWF are trace quantities of mouse immunoglobulin (IgG, from the immunoaffinity purification), host cell (i.e., CHO) protein, rFurin (used to further process rVWF), and recombinant factor VIII (rFVIII).

Von Willebrand factor is a large multimeric glycoprotein that is normally found in plasma, and stored as ultra-large multimers in alpha-granules of platelets and intracellular organelles known as Weibel-Palade bodies, prior to secretion into the blood.^1 Once the VWF is released to the blood stream and in contact with ADAMTS13 (a proteolytic enzyme in blood), it is cleaved to smaller sizes that can be detected with SDS agarose gels as multimer bands, representing the various species of VWF within the circulation. VONVENDI is rVWF that contains ultra-large multimers in addition to all of the multimers found in plasma as it is not exposed to proteolysis by ADAMTS13 during the manufacturing process.

VONVENDI is formulated as a sterile, non-pyrogenic, white to off-white friable powder for intravenous injection after reconstitution. VONVENDI in a single-dose vial contains nominally 650 or 1300 IU VWF:RCo.

The product contains no preservative. When reconstituted with the provided Sterile Water for Injection the final solution contains the following stabilizers and excipients (Table 6) in targeted amounts:

Table 6: Concentration of Stabilizer and Excipient after Reconstitution
Stabilizer and Excipient | Targeted Concentration for Nominal Strengths (650, 1300 IU)
Tri-Sodium Citrate-dihydrate | 15 mM
Glycine | 15 mM
Mannitol | 20 g/L
Trehalose-dihydrate | 10 g/L
Polysorbate 80 | 0.1 g/L

Each vial of VONVENDI is labeled with the specific number of units of VWF:RCo expressed in IU, which are based on the current World Health Organization (WHO) standard for VWF concentrate. After reconstitution of the lyophilized powder and filtration/withdrawal into a syringe, all dosage strengths yield a clear, colorless solution, free from particles.

12 CLINICAL PHARMACOLOGY

12.1 Mechanism of Action

In VWD patients, VONVENDI acts 1) to promote hemostasis by mediating platelet adhesion to damaged vascular sub-endothelial matrix (e.g., collagen) and platelet aggregation, and 2) as a carrier protein for factor VIII, protecting it from rapid proteolysis. The adhesive activity of VWF depends on the size of its multimers, with larger multimers being the most effective in supporting interactions with collagen and platelet receptors.^1 The binding capacity and affinity of VONVENDI to factor VIII in plasma is comparable to that of endogenous VWF, allowing for VONVENDI to reduce factor VIII clearance.

12.2 Pharmacodynamics

The PD of VWF following prophylactic treatment with VONVENDI in adults were investigated in a clinical trial (Study 5). In Prior OD adult patients, a single infusion of VONVENDI led to an increase of FVIII:C with peak levels observed approximately 24 hours post-infusion (mean [SD] dose: 50.1 [3.03] IU/kg). After 1-year repeat infusions of 50 ± 10 IU/kg VONVENDI twice weekly, the median (range) pre-dose FVIII:C increased from 2.0 (2.0 to 45.0) IU/dL (baseline after wash-out, N=12) to 11.0 (6.0 to 81.0) IU/dL (Month 12, N=9). The pre-dose FVIII:C (median [range] ≥11.0 [10.0 to 81.0] IU/dL) were observed over the prophylactic visits at Months 1, 2, 3, 6, 9 and 12. At Month 12, the median [range] Cmax and AUC(0-96 hours) of FVIII:C were 97.0 [63.0, 169.0] IU/dL and 5752 [2870, 11400] IU*h/dL (N=9), respectively.

The PD of VWF in 20 pediatric patients (aged less than 17 years) receiving on-demand therapy for bleeding episodes and treatment for surgical bleeds were evaluated using sparse sampling across three age groups (less than 6 years old, 6 years to less than 12 years old, and 12 years to less than 17 years old). Following a single infusion of VONVENDI at 50 (±5) IU/kg in pediatric patients, the median baseline corrected Cmax and AUC0-96 of FVIII:C were 64.5 IU/dL and 3379 IU*h/dL.

12.3 Pharmacokinetics

The PK profile of VONVENDI was determined based on data analyses from two clinical trials in adults (Studies 1 and 2) by assessment of VWF:RCo, VWF:Ag, and VWF:CB following a single dose. Patients were evaluated in the non-bleeding state.

Table 7 below summarizes the PK parameters of VONVENDI after infusions of 50 IU/kg (PK50) or 80 IU/kg VWF:RCo (PK80) VONVENDI in adult patients.

Table 7: Pharmacokinetic Assessment of VWF:RCo Following Single-Dose Infusion in Adults
Parameter (unit) | PK50 VONVENDI with ADVATE [This study was conducted using VONVENDI (recombinant VWF) and ADVATE [Antihemophilic factor (recombinant)], a recombinant factor VIII.] | PK50 VONVENDI | PK80 VONVENDI
Parameter (unit) | Mean (SD) Min; Max | Mean (SD) Min; Max | Mean (SD) Min; Max
T1/2 | 19.3 (10.99) | 22.6 (5.34) | 19.1 (4.32)
(h) | 10.8; 51.2 | 17.0; 37.2 | 11.8; 28.0
CL | 0.04 (0.028) | 0.02 (0.005) | 0.03 (0.009)
([dL/kg]/h) | 0.01; 0.16 | 0.02; 0.04 | 0.02; 0.05
IR | 1.7 (0.62) | 1.9 (0.41) | 2.0 (0.39)
([IU/dL]/([IU/kg]) | 1.0; 3.6 | 1.2; 2.7 | 1.4; 2.9
AUC0-inf | 1541.4 (554.31) | 2105.4 (427.51) | 2939.0 (732.72)
(IU*h/dL) | 173.8; 2862.0 | 1334.0; 2813.3 | 1507.8; 4121.1
AUC0-inf/Dose | 33.4 (13.87) | 42.1 (8.31) | 36.8 (8.97)
([IU*h/dL]/[IU/kg]) | 6.4; 70.4 | 27.8; 54.8 | 18.8; 50.4
AUC(0-inf) = area under plasma concentration-time curve from time 0 hour to infinite time post-infusion; IR = incremental recovery; CL = clearance; t1/2 = half-life.

The PK of VWF following prophylactic treatment with VONVENDI in adults were investigated in a clinical trial (Study 5). Steady state PK parameters of VWF:RCo are presented in Table 8 for patients who were previously treated on-demand (OD) with any VWF product prior to study entry (Prior OD group) and patients who were previously treated prophylactically with a plasma derived VWF product (Switch group) prior to study enrollment. The pharmacokinetics of VWF following single and multiple dosing (at Month 12) were similar in the Prior OD group. The PK of VWF following multiple dosing (at 12 months) were similar between Prior OD and Switch groups.

Table 8: Steady State Pharmacokinetic Assessment of VWF:RCo (Month 12; All Patients)
Parameter (unit) | Prior OD Group N=9 Mean (SD) Min; Max | Switch Group N=7 Mean (SD) Min; Max
T1/2 | 16.5 (4.13) [N=7] | 15.1 (5.78) [N=5]
(h) | 10.9; 22.4 | 9.4; 22.9
CL | 0.04 (0.012) | 0.04 (0.014)
([dL/kg]/h) | 0.02; 0.05 | 0.02; 0.06
IR at Cmax | 1.8 (0.5) | 1.9 (0.29)
([IU/dL] / [IU/kg]) | 0.9; 2.7 | 1.6; 2.3
Cmax | 92.6 (37.1) | 102.9 (44.7)
(IU/dL) | 41.6; 148.7 | 46.7; 176.6
Cmax/Dose | 1.9 (0.6) | 1.9 (0.3)
([IU/dL]/[IU/kg]) | 0.9; 2.7 | 1.6; 2.3
AUC(0-96 hours) | 1561 (1298) | 1662 (675) [N=3]
(IU*h/dL) | 460; 4460 | 1230; 2440
AUC(0- 96 hours)/Dose | 30.9 (23.4) | 27.5 (9.7)
([IU*h/dL]/[IU/kg]) | 9.8; 83.4 | 21.7; 38.7
AUC(0-96 hours) = area under plasma concentration-time curve from time 0 to 96 hours post-infusion; Cmax = maximum plasma concentration; IR = incremental recovery; CL = clearance; t1/2 = half-life; dose regimens for patients with VWD in Prior OD group were 41 to 56 IU/kg and for patients with VWD in Switch group were 24 to 77 IU/kg.

The pharmacokinetics of VWF in pediatric patients with VWD were estimated based on PK modeling using sparse PK samples collected during a pediatric clinical trial (Study 3) across three age groups (less than 6 years old [N=5], 6 years to less than 12 years old [N=10], and 12 years to less than 17 years old [N=6]) receiving 50 ± 5 IU/kg rVWF:RCo VONVENDI (Table 9).

Table 9: Pharmacokinetic Assessment of VWF:RCo Following Single-Dose Infusion in Pediatric Patients
Parameter (unit) Age Range | PK50 VONVENDI Mean (SD) Min; Max <6 yrs (n=5) | PK50 VONVENDI Mean (SD) Min; Max 6 yrs to <12 yrs (n=10) | PK50 VONVENDI Mean (SD) Min; Max 12 yrs to <17 yrs (n=6) | PK50 VONVENDI Mean (SD) Min; Max Total (n=21)
T1/2 | 12.4 (2.90) | 14.5 (1.47) | 14.5 (1.27) | 14.0 (1.96)
(h) | 8.96; 15.7 | 12.3; 16.7 | 13.0; 16.4 | 8.96; 16.7
CL | 0.08 (0.041) | 0.05 (0.016) | 0.05 (0.008) | 0.06 (0.026)
([dL/kg]/h) | 0.048; 0.141 | 0.032; 0.077 | 0.034; 0.055 | 0.032; 0.141
Cmax | 69.4 (18.8) | 82.6 (20.8) | 80.8 (19.7) | 79.0 (19.9)
(IU/dL) | 51.0; 90.3 | 53.7; 122 | 65.7; 115 | 51.0; 122
IR at Cmax | 1.25 (0.378) | 1.54 (0.378) | 1.57 (0.279) | 1.48 (0.360)
([IU/dL]/[(IU/kg]) | 0.828; 1.78 | 1.06; 2.13 | 1.29; 2.06 | 0.828; 2.13
AUC0-inf | 1260 (654) | 1630 (882) | 1600 (867) | 1530 (805)
(IU*h/dL) | 811; 2390 | 697; 3360 | 961; 2760 | 697; 3360
AUC0-inf/Dose | 25.6 (12.8) | 32.5 (18.1) | 33.1 (17.6) | 31.0 (16.3)
([IU*h/dL]/[IU/kg]) | 16.1; 47.9 | 13.5; 68.5 | 19.0; 55.6 | 13.5; 68.5
AUC(0-inf) = area under plasma concentration-time curve from time 0 hour to infinite time post-infusion; IR = incremental recovery; CL = clearance; t1/2 = half-life.

12.6 Immunogenicity

The immunogenicity of VONVENDI was assessed in clinical trials by assessing the development of neutralizing antibodies against VWF and FVIII, as well as binding antibodies against VWF, Furin, Chinese hamster ovary (CHO) protein and mouse IgG. Of the 132 patients who received VONVENDI in the clinical trials, one patient who was treated with VONVENDI perioperatively developed treatment-emergent binding antibodies against VWF following a surgery, for whom no adverse events or lack of hemostatic efficacy was reported. No binding antibodies against potential impurities such as rFurin, CHO-protein or mouse IgG developed after treatment with VONVENDI.

Two patients included in the surgery study had pre-existing high-titer specific binding antibodies against VWF. The high-titer binding anti-VWF antibodies were associated with a significantly decreased VWF:Ag activity post-infusion of either plasma derived VWF (pdVWF) or rVWF and consequently, the decreased activity of VWF:RCo, VWF:CB and FVIII:C. This finding indicates the potential clinical significance of pre-existing binding (non-neutralizing) antibodies: VWD patients previously treated with pdVWF concentrates may be at risk to express a pre-existing binding antibody against VWF prior to first exposure to rVWF which could potentially result in a decreased hemostatic response to rVWF. Such patients could be managed clinically by administration of higher doses of rVWF based on the PK data for each individual patient.

13 NONCLINICAL TOXICOLOGY

13.1 Carcinogenesis, Mutagenesis, Impairment of Fertility

In vitro and in vivo genotoxicity studies indicated no mutagenic potential for VONVENDI. Long-term animal studies to assess the carcinogenic potential of VONVENDI were not performed. Animal studies evaluating the developmental and reproductive toxicity of VONVENDI were not conducted.

14 CLINICAL STUDIES

The efficacy of VONVENDI was evaluated in Study 1 (NCT00816660), Study 2 (NCT01410227), Study 3 (NCT02932618), Study 4 (NCT02283268), Study 5 (NCT02973087), and Study 6 (NCT03879135), as described below.

Study 1

This was a multicenter, single-blind, randomized, controlled, dose escalation study to evaluate the pharmacokinetics (PK), safety and tolerability of VONVENDI in patients with severe von Willebrand disease (VWD). The study enrolled patients with type 3 or severe type 1 VWD (VWF:RCo ≤10% and FVIII<20%), and who had a history of ≥25 days of exposure to VWF/FVIII factor concentrates.

A total of 31 patients received a single infusion of VONVENDI and rFVIII in a ratio of 1.3:1. VONVENDI was administered at a dose of either 2, 7.5, 20, or 50 IU/kg. The major outcome measures were PK parameters as described in section 12 above [see Clinical pharmacology (12.3)].

On-Demand Treatment and Control of Bleeding Episodes

Study 2 (Adults)

Hemostatic efficacy of VONVENDI was assessed in a multicenter, open-label trial investigating different dosing strategies with and without rFVIII (ADVATE) for on-demand treatment and control of bleeding episodes in adults diagnosed with von Willebrand disease. The study enrolled 37 patients who received treatment for on-demand treatment and control of bleeding episodes.

The demographic of the population were as follows: median age of 37 years (range 18 to 64), 20 patients (54%) were female, 32 patients (86%) were White, 5 patients (14%) were Asian and 2 patients (5%) were of Hispanic or Latino ethnicity. The types of VWD were as follows: Type 1 (n=2; 5%), Type 2A (n=5; 14%), Type 2N (n=1; 3%). and Type 3 (n=29; 78%).

Bleeding episodes were treated initially with an infusion of VONVENDI and ADVATE at a ratio of 1.3:1 respectively (i.e., 30% more VONVENDI than ADVATE), and subsequently with VONVENDI with or without ADVATE. ADVATE was given based on FVIII:C levels with a goal to achieve target plasma levels of greater than 40 IU/dL (40%) of FVIII:C.

A total of 192 bleeding episodes were treated with VONVENDI in 22/37 adult patients. The median cumulative dose of VONVENDI administered per bleeding episode (with or without ADVATE) was 48.2 IU/kg (90% CI, 43.9 to 50.2) IU/kg. The median number of VONVENDI infusions was 2 for major/severe (range: 1 to 3), 1 for moderate (range: 1 to 4), and 1 for minor bleeding episodes (range: 1 to 3). The median cumulative dose based on bleeding severity was 100 IU/kg (range, 57.5 to 135 IU/kg) for major (n=7), 52.7 IU/kg (range, 23.8 to 184.9 IU/kg) for moderate (n=61), and 43.3 IU/kg (range: 25.2 to 158.2 IU/kg) for minor bleeding episodes (n=122).

The primary efficacy endpoint was the number of patients with treatment success for control of bleeding episodes. Treatment success was defined as a mean efficacy rating score of less than 2.5 for all bleeding episodes treated with VONVENDI (with or without ADVATE) during the trial period, using a pre-specified 4-point rating scale comparing the prospectively estimated number of infusions needed to treat the bleeding episodes as assessed by the investigator to the actual number of infusions administered. The definitions for each of the 4-point rating scales are provided in Table 10.

Table 10: Definitions of 4-Point Rating Scales
Rating | Minor and Moderate Bleeding Events | Major Bleeding Events
Excellent (= 1) | Actual number of infusions ≤ estimated number of infusions required to treat that bleeding episode. No additional VWF coagulation factor containing product required. | Actual number of infusions ≤ estimated number of infusions required to treat that bleeding episode. No additional VWF coagulation factor containing product required.
Good (= 2) | 1 to 2 infusions greater than estimated required to control that bleeding episode. No additional VWF coagulation factor containing product required. | <1.5x infusions greater than estimated required to control that bleeding episode. No additional VWF coagulation factor containing product required.
Moderate (= 3) | 3 or more infusions greater than estimated used to control that bleeding event. No additional VWF coagulation factor containing product required. | ≥1.5x more infusions greater than estimated used to control that bleeding event. No additional VWF coagulation factor containing product required.
None (= 4) | Severe uncontrolled bleeding or intensity of bleeding not changed. Additional VWF coagulation factor containing product required. | Severe uncontrolled bleeding or intensity of bleeding not changed. Additional VWF coagulation factor containing product required.

Secondary efficacy measures were the number of treated bleeding episodes with an efficacy rating of “excellent” or “good”, the number of infusions and number of units of VONVENDI, administered with or without ADVATE, per bleeding episode.

The primary efficacy assessment excluded patients with GI bleeds (n=2), and patients in whom the number of infusions required per bleeding episode was estimated retrospectively (n=2). The rate of patients (n=18) with treatment success was 100% (95% CI, 81.5 to 100). Sensitivity analyses of treatment success for bleeding episodes including GI bleeds and those bleeding episodes for which the investigator had to make retrospective assessment of the number of infusions required (n=22: 17 with type 3 VWD, 4 with type 2A VWD and 1 with type 2N VWD) confirmed the primary analysis, with a 100% treatment success rate for each scenario.

All bleeding episodes treated with VONVENDI and ADVATE or VONVENDI alone received an efficacy rating of excellent (97%) or good (3%). This was consistent across all degrees of severity.

Table 11 summarizes data obtained for number of infusions and efficacy rating per bleeding episode by location. Bleeding episodes of “Other” location (n=37) are not included in the table.

Table 11: Efficacy by Bleeding Episode Location (Adults)
Bleeding Episodes by Location (n) [A single bleeding episode may occur and be counted in multiple locations] | Median Number of Infusions (Range) | Rating (%)
Joint (n=59) | 1 (1 to 3) | Excellent (97%) Good (3%)
GI (n=6) | 1 (1 to 2) | Excellent (83%) Good (17%)
Mucosal: Genital Tract Female (n=32) | 1 (1 to 2) | Excellent (97%) Good (3%)
Mucosal: Nasopharyngeal (n=42) | 1 (1 to 2) | Excellent (98%) Good (2%)
Mucosal: Mouth and Oral Cavity (n=26) | 1 (1 to 4) | Excellent (100%) Good (0%)

Study 3 (Pediatrics)

Hemostatic efficacy of VONVENDI with or without ADVATE for on-demand treatment of non-surgical bleeding episodes was assessed in a multicenter, open-label trial in pediatric patients diagnosed with severe VWD. The study enrolled 18 patients who received treatment for on-demand bleeding episodes, including 3 patients who were 17 years old. The patients were followed for a duration of at least 12 months.

The demographics of the population were as follows: the median age was 11 years (range 1 to 17 years), 11 patients (61%) were female, 15 patients (94%) were White, 1 patient (6%) was of multiple races, and 1 patient (6%) was Hispanic or Latino. The types of VWD were as follows: Type 1 (n=2; 11%), Type 2A (n=3; 17%), Type 2B (n=2; 11%), and Type 3 (n=11; 61%).

A total of 28 bleeding episodes in 7 patients were treated with an initial dose of 40 to 60 IU/kg VONVENDI (median dose of 48 IU/kg; range 18 to 63 IU/kg) along with 30 to 45 IU/kg ADVATE (median dose of 33 IU/kg; range 9 to 45 IU/kg). A total of 76 bleeding episodes in 15 patients received an initial dose of 40 to 60 IU/kg VONVENDI (median dose 49 IU/kg; range 18 to 86 IU/kg) without ADVATE due to baseline FVIII level of at least 30%. In 8 patients, at least one additional dose of VONVENDI without ADVATE was administered in 18 bleeding episodes every 8 to 24 hours to maintain VWF:RCo and FVIII levels.

The primary efficacy endpoint was the number of patients with treatment success. Treatment success was defined as a mean efficacy rating score of less than 2.5 for all bleeding episodes using the pre-specified 4-point efficacy rating scale. Secondary efficacy outcome measures were assessed for each bleeding episode and included the number of treated nonsurgical bleeding episodes with an efficacy rating of “excellent” or “good”, the number of infusions, and VONVENDI and ADVATE consumption.

Table 12 summarizes efficacy rating and VONVENDI consumption by bleeding episode severity.

Table 12: Efficacy by Severity of Bleeding Episodes (Pediatric On-Demand)
- | Mild Severity | Moderate Severity | Major/Severe Severity | Unknown Severity | Total Severity
Number of Patients with Bleeding Episodes | 13 | 13 | 2 | 3 | 18
Number of Treated Nonsurgical Bleeding Episodes (n) [Bleeding episodes were treated with VONVENDI, with or without ADVATE (a patient could have bleeding episodes treated with VONVENDI alone or with both VONVENDI and ADVATE).] | 48 | 31 | 2 | 23 | 104
Hemostatic Efficacy Rating Counts (%) [Counts and percentages are based on bleeding episodes with known hemostatic efficacy ratings.] | Excellent 48 (100) | Excellent 29 (97) Good 1 (3) | Excellent 2 (100) | Excellent 18 (100) | Excellent 97 (99) Good 1 (1)

Table 13 summarizes efficacy rating by location of the bleeding episode.

Table 13: Efficacy by Bleeding Episode Location (Pediatric On-Demand)
Bleeding Episodes by Location (n) | Median Number of Infusions of rVWF (Range) | Median Number of Infusions of ADVATE (Range) | Rating (%)
Joint (n=17) | 1 (1 to 9) | 1 (1 to 1) | Excellent (100%) Good (0%)
Mucosal: Nasopharyngeal (n=25) | 1 (1 to 3) | 1 (1 to 1) | Excellent (100%) Good (0%)
Mucosal: Mouth and Oral Cavity (n=14) | 1 (1 to 3) | NA | Excellent (93%) Good (7%)
Mucosal: Genital Tract Female (n=12) | 1 (1 to 1) | 1 (1 to 1) | Excellent (100%) Good (0%)
Muscle/Skin/Soft Tissue (n=14) | 1 (1 to 3) | 1 (1 to 1) | Excellent (100%) Good (0%)
Multiple/Other (n=21) | 1 (1 to 2) | 1 (1 to 1) | Excellent (100%) Good (0%)

Perioperative Management of Bleeding

Study 4 (Adults)

Hemostatic efficacy of VONVENDI was assessed in a prospective, open-label, multicenter trial to evaluate efficacy and safety of VONVENDI with or without ADVATE in elective surgical procedures in adults diagnosed with severe VWD and the patients were followed for 14 days after surgery. A total of 15 VWD patients completed the trial. Out of 15 patients, 10 underwent major surgeries and five underwent minor surgeries.

The demographics of the population were as follows: Median age was 40 (range, 20 to 70 years), 8 patients (53%) were female, 12 patients (80%) were White, 3 patients (20%) were Asian and 1 patient (7%) was Hispanic or Latino. The types of VWD were as follows: Type 1 (n=3; 20%), Type 2A (n=2; 13%), Type 2B (n=1; 7%), Type 2M (n=1; 7%) and Type 3 (n=8; 53%).

Major surgeries included orthopedic surgeries: total hip replacement, total knee replacement, knee endoprosthesis, ankle prosthesis, anterior cruciate ligament surgery and meniscectomy. Other major surgeries included laparoscopic cholecystectomy, laparoscopic cystectomy and complex dental extractions. Minor surgeries/procedures included nasopharyngoscopy, dental extractions, colonoscopy and radioisotope synovectomy.

All patients were administered a 12 to 24 hour preoperative dose of 40 to 60 IU/kg of VONVENDI to increase the factor VIII levels to target levels. Within 3 hours prior to surgery, the patients’ FVIII:C levels were assessed to ensure that target of 30 IU/dL for minor surgeries and 60 IU/dL for major surgeries was achieved. Within 1 hour prior to surgery, patients received a dose of VONVENDI. ADVATE (recombinant Factor VIII) was administered based on FVIII:C levels performed 3 hours prior to surgery. VWF and factor VIII IR were used to guide the initial and subsequent doses.

The primary outcome measure was the overall hemostatic efficacy assessed 24 hours after the last perioperative VONVENDI infusion or at completion of study visit whichever occurred earlier using a 4-point ordinal efficacy scale outlined in Table 14 (“excellent”, “good”, “moderate” and “none”) based on estimated expected versus actual blood loss, transfusion requirements and postoperative bleeding and oozing. A rating of excellent or good was required to declare the outcome a success.

Table 14: Primary Efficacy Assessment
Rating | Overall Assessment of Hemostatic Efficacy 24 Hours after Last Perioperative IP Infusion or at Day 14 Completion Visit (Whatever Occurs Earlier)
Excellent (1) | Intra- and postoperative hemostasis achieved with rVWF with or without ADVATE was as good or better than that expected for the type of surgical procedure performed in a hemostatically normal patient.
Good (2) | Intra- and postoperative hemostasis achieved with rVWF with or without ADVATE was probably as good as that expected for the type of surgical procedure performed in a hemostatically normal patient.
Moderate (3) | Intra- and postoperative hemostasis with rVWF with or without ADVATE was clearly less than optimal for the type of procedure performed but was maintained without the need to change the rVWF concentrate.
None (4) | Patient experienced uncontrolled bleeding that was the result of inadequate therapeutic response despite proper dosing, necessitating a change of rVWF concentrate.

Overall hemostatic efficacy for major and minor surgeries was 100% (15/15) with a 90% confidence interval of 81.9% to 100%. It was excellent for 60% of surgeries and good for 40% of surgeries.

Intraoperative hemostatic efficacy was a secondary endpoint. For major and minor surgeries, it was 100% with a 90% confidence interval of 81.9% to 100%. It was excellent for 73% of surgeries and good for 27% of surgeries.

For details regarding hemostatic efficacy for minor and major surgery, see Table 15.

Table 15: Overall Hemostatic Efficacy (Adults)
Type of Surgery | Excellent 9/15 (60%) | Good 6/15 (40%) | Moderate 0/15 (0.0%) | Total N=15
Minor | 4 | 1 | 0 | 5
Major | 5 | 5 | 0 | 10

Dosing was individualized based on IR results performed before surgery.

Mean total 12 to 24 preoperative dose was 50.9 IU/kg (median 55.0 IU/kg; range, 36.1 to 59.9 IU/kg).

Mean total loading dose (1 hour preoperative dose) per infusion was 38.6 IU/kg (median 35.8 IU/kg; range, 8.0 to 82.7 IU/kg). Major surgeries required a mean loading dose of 42.8 IU/kg (median 37.6 IU/kg; range, 15.7 to 82.7 IU/kg) in comparison with a mean loading dose of 30.2 IU/kg (median 34.2 IU/kg; range, 8.0 to 46.4 IU/kg) for minor surgeries.

For patients treated with VONVENDI (with or without ADVATE), the median total postoperative dose within the first 7 days after surgery was 114.2 IU/kg with a range of 23.8 to 318.9 IU/kg (n=13) and 76.2 IU/kg with a range of 23.8 to 214.4 IU/kg for the next 7 postoperative days (n=8).

Study 3 (Pediatrics)

The multicenter, open-label pediatric trial (Study 3) also assessed the efficacy of VONVENDI with or without ADVATE in the management of surgical bleeding from elective and emergency surgeries in pediatric patients diagnosed with severe von Willebrand disease. A total of 4 patients completed the study. Four minor (three elective and one emergency) surgeries were treated with VONVENDI in these four patients, aged 6 to 12 years.

Of the 4 patients who underwent surgeries, 2 were 12 to <17 years, and 2 were 6 to <12 years, and no subjects were <6 years. Three were male subjects with one female undergoing emergency surgery. All patients were White and /non-Hispanic or Latino and 1 had Type 1 VWD and 3 had Type 3 VWD.

Minor surgeries included second stage buccal mucosa hypospadias reconstruction, tunneled central venous catheter with subcutaneous port removal (emergency surgery), and circumcision.

The mean dose of VONVENDI administered preoperatively and postoperatively during the 4 surgeries was 94 IU/kg (mean, 1.8 preoperative infusions) and 117 IU/kg (mean, 2.3 postoperative infusions), respectively. A total of 5 infusions of ADVATE were administered for one surgery in one patient. This patient received one preoperative infusion and 4 postoperative infusions.

All 4 surgeries had overall and intraoperative hemostatic efficacy ratings of “Excellent” (95% CI [39.8, 100.0]). The blood loss rating (actual versus predicted blood loss) was “Excellent” for all 4 surgeries.

Routine Prophylaxis to Reduce the Frequency of Bleeding Episodes

Study 5 (Adults)

VONVENDI was assessed in a prospective, single arm, open-label, international multicenter study (Study 5) to evaluate efficacy, safety, PK and PD of prophylactic treatment in reducing the frequency of bleeding episodes in adult patients (age 18 years and older) diagnosed with VWD. Patients were enrolled into two treatment arms based on the treatment they received for management of bleeding prior to study entry consisting of a Prior on-demand (OD) group in which patients received on-demand treatment only and the Switch group in which patients had received prophylactic treatment with pdVWF. Efficacy was assessed based on the annualized bleeding rate for all bleeds, spontaneous bleeds and joint bleeds and was based on descriptive statistics.

The study enrolled 23 patients who received prophylactic treatment. Twenty-two efficacy evaluable patients received a median of 92.5 doses, 12 of these patients had previously received on demand treatment (Prior OD group) and 10 patients previously received prophylactic treatment with pdVWF (Switch group) prior to enrolling into this study. Nine patients in the Prior OD group and 8 patients in the Switch group completed the study which required 12 months of treatment.

The demographic of the population is as follows: Median age of patients in the study was 34 years (18 - 77 years), 12 patients (55%) were male, 21 patients (95%) were White and 19 patients (86%) were non-Hispanic or Latino. Of the 12 patients in the Prior OD group, one had severe Type 1, one had severe Type 2 VWD, and ten had severe Type 3 VWD. Of the 10 patients in the Switch group, one had severe Type 1, one had severe Type 2 VWD, and eight had severe Type 3 VWD.

Patients in the Prior OD group began treatment at 50 ± 10 IU/kg per infusion twice weekly and in the Switch group, the initial VONVENDI prophylactic treatment was based on matching (±10%) VWF content of the patient’s prior pdVWF prophylaxis regimen. The initial prophylactic regimen for 80% of Switch patients was also twice weekly, except for 2 patients; one started with a once weekly regimen of 80 IU/kg/infusion and the other started with 3-times-per-week regimen of 60 IU/kg/infusion. Dose adjustments up to 80 IU/kg per infusion and/or higher frequency up to 3 infusions per week were allowed in cases of breakthrough bleeding episodes.

The mean (SD) [range] average weight-adjusted VONVENDI prophylaxis dose per infusion was 52.2 (3.8) [44.8, 58.8] IU/kg for Prior OD patients and 52.2 (16.2) [24.4, 79.4] IU/kg for Switch patients. The mean (SD) number of prophylaxis infusions per week were 1.88 (0.7) for Prior OD and 1.85 (0.4) for Switch patients.

For the Prior OD group, treatment success was defined as at least 25% reduction in the ABR for spontaneous bleeding episodes requiring factor treatment from the patient’s historical to the on-study period (reduction success). A total of 11/12 (91.7%) Prior OD patients achieved ABR reduction success.

For the Switch group, treatment success was defined as achieving an on-study ABR for spontaneous bleeding episodes requiring factor treatment that was no greater than the patient’s historical ABR for treated bleeding episodes (preservation success). A total of 9/10 (90%) Switch patients achieved preservation success.

The efficacy parameters of VONVENDI as prophylactic treatment in adult patients are provided in Table 16.

Table 16: Efficacy of Routine Prophylaxis with VONVENDI
Bleeding Event | Pre-Study ABR [Based on descriptive statistics.] , [Based on bleeding and treatment history documented in medical records prior to the study.] | On-Study ABR
Bleeding Event | Median (Min, Max) | Median (Min, Max)
Prior OD Patients (N = 12) | - | -
Treated Spontaneous and Traumatic Bleeds | 4.0 (3.0, 156.0) | 0.0 (0.0, 5.8)
All Spontaneous and Traumatic Bleeds [Includes treated and untreated bleeding events.] | 4.5 (3.0, 159.0) | 0.5 (0.0, 158.0)
All Joint Bleeds, [All joint bleeds in Prior OD patients were treated.] | 1.5 (0.0, 7.0) | 0.0 (0.0, 1.9)
Switch Patients (N=10) | - | -
Treated Spontaneous and Traumatic Bleeds | 0.0 (0.0, 47.0) | 0.0 (0.0, 12.1)
All Spontaneous and Traumatic Bleeds | 1.0 (0.0, 47.0) | 3.6 (0.0, 27.0)
All Joint Bleeds | 0.0 (0.0, 1.0) | 0.0 (0.0, 2.0)

15 REFERENCES

1 Stockschlaeder M, Schneppenheim R, Budde U, Update on von Willebrand factor multimers: focus on high-molecular-weight multimers and their role in hemostasis. Blood Coagul Fibrinolysis 2014, 25:206-216.

16 HOW SUPPLIED/STORAGE AND HANDLING

How Supplied

VONVENDI is packaged with Sterile Water for Injection (sWFI), one Mix2Vial reconstitution device, one full prescribing physician insert, and one patient insert.

VONVENDI is available in single-dose vials that contain the following product strengths:

Color Code | VWF:RCo Potency Range | Carton NDC | sWFI fill size
Green | 450–850 IU per vial | 0944-7551-02 | 5 mL
Dark Red | 900–1700 IU per vial | 0944-7553-02 | 10 mL

The actual von Willebrand factor activity in international units is printed on the label of each VONVENDI vial and carton.

Components are not made with natural rubber latex.

Storage and Handling

- Store at refrigerated temperature 2°C to 8°C (36°F to 46°F) or room temperature not to exceed 30°C (86°F).
- Do not freeze.
- Store in the original box and protect from extreme exposure to light.
- Do not use beyond the expiration date printed on the VONVENDI vial label or carton.
- Do not use if the solution in the syringe is cloudy or contains flakes or particles after filtration from the vial into the syringe.
- Use reconstituted product immediately or within 3 hours after reconstitution.
- Discard any unused reconstituted product after 3 hours.

17 PATIENT COUNSELING INFORMATION

Advise the patient and/or caregiver:

- To read the FDA-approved patient labeling (Patient Information and Instructions for Use).
- About early signs of hypersensitivity and infusion-related reactions, including anaphylactic shock, generalized urticaria, angioedema, chest tightness, hypotension, shock, lethargy, nausea, vomiting, paresthesia, pruritus, restlessness, wheezing and/or acute respiratory distress. Advise patients and/or caregivers to discontinue use of the product if these symptoms occur and seek immediate emergency treatment with resuscitative measures.
- To contact their physician or treatment center for further treatment and/or assessment if they experience a lack of clinical response to von Willebrand factor therapy, as this may be a manifestation of an inhibitor.
- To consult with their physicians or healthcare provider prior to travel. While traveling, advise patients and/or caregivers to bring an adequate supply of VONVENDI based on their current regimen of treatment.

Manufactured by:
Takeda Pharmaceuticals U.S.A., Inc.
Cambridge, MA 02142
U.S. License No. 1898

VONVENDI is a registered trademark of Baxalta Incorporated.

Takeda and are registered trademarks of Takeda Pharmaceutical Company Limited.

Mix2Vial® is a registered trademark of West Pharma. Services IL, Ltd., a subsidiary of West Pharmaceutical Services, Inc.

Patented: see www.takeda.com/en-us/patents

©2025 Takeda Pharmaceutical Company Limited. All rights reserved.

VON355

Patient Information
VONVENDI®
[von Willebrand factor (recombinant)]

This leaflet summarizes important information about VONVENDI. Please read it carefully before using this medicine. This information does not take the place of talking with your healthcare provider, and it does not include all of the important information about VONVENDI. If you have any questions after reading this, ask your healthcare provider.
Do not attempt to do an infusion to yourself unless you have been taught how by your healthcare provider or hemophilia center.
You must carefully follow your healthcare provider’s instructions regarding the dose and schedule for infusing VONVENDI so that your treatment will work best for you.

What is VONVENDI?
VONVENDI is a recombinant medicine used to replace low levels or not properly working von Willebrand factor in people with von Willebrand disease. Von Willebrand disease is an inherited bleeding disorder in which blood does not clot normally.
VONVENDI is used in adults and children diagnosed with von Willebrand disease to:

- treat and control bleeding episodes
- prevent excessive bleeding during and after surgery

For adult patients only:

- reduce the number of bleeding episodes when used regularly (prophylaxis)

Who should not use VONVENDI?
You should not use VONVENDI if you:

- Are allergic to any ingredients in VONVENDI.
- Are allergic to mice or hamsters.

Tell your healthcare provider if you are pregnant or breastfeeding because VONVENDI may not be right for you.

What should I tell my healthcare provider before I use VONVENDI?
You should tell your healthcare provider if you:

- Have or have had any medical problems.
- Take any medicines, including prescription and non-prescription medicines, such as over-the-counter medicines, supplements or herbal remedies.
- Have any allergies, including allergies to mice or hamsters.
- Are breastfeeding. It is not known if VONVENDI passes into your milk and if it can harm your baby.
- Are pregnant or planning to become pregnant. It is not known if VONVENDI can harm your unborn baby.
- Have been told that you have inhibitors to von Willebrand factor (because VONVENDI may not work for you).
- Have been told that you have inhibitors to blood coagulation factor VIII.

How should I use VONVENDI?
VONVENDI is given directly into the bloodstream. Your first dose of VONVENDI for each bleeding episode may be administered with a recombinant factor VIII (factor VIII not produced from plasma) as instructed by your healthcare provider.
Your healthcare provider will instruct you whether additional doses of VONVENDI with or without recombinant factor VIII are needed.
You may infuse VONVENDI at a hemophilia treatment center, at your healthcare provider’s office or in your home. You should be trained on how to do infusions by your healthcare provider or hemophilia treatment center. Many people with von Willebrand disease learn to infuse VONVENDI by themselves or with the help of a family member.
Your healthcare provider will tell you how much VONVENDI to use based on your weight, the severity of your von Willebrand disease, and where you are bleeding.
Call your healthcare provider right away if your bleeding does not stop after taking VONVENDI.
Use the reconstituted product (after mixing dry product with the supplied sterile water) immediately. If not, store at room temperature not to exceed 25°C (77°F) for up to 3 hours. Discard after 3 hours.

What are the possible side effects of VONVENDI?
You can have an allergic reaction to VONVENDI.
Call your healthcare provider right away and stop treatment if you get a rash or hives, itching, tightness of the throat, chest pain or tightness, difficulty breathing, lightheadedness, dizziness, nausea or fainting.
Side effects that have been reported with VONVENDI include: headache, nausea, vomiting, tingling or burning at infusion site, chest discomfort, dizziness, hot flashes, itching, high blood pressure, muscle twitching, unusual taste, blood clots and increased heart rate. These are not all the possible side effects with VONVENDI. You can ask your healthcare provider for information that is written for healthcare professionals.
Tell your healthcare provider about any side effects that bother you or do not go away.

What are the VONVENDI dosage strengths?
VONVENDI with Sterile Water for Injection and Mix2Vial reconstitution device comes in two different dosage strengths.

Green: Dosage strength of approximately 650 International Units (450–850 IU) (reconstituted with 5 mL of sterile water).

Dark Red: Dosage strength of approximately 1300 International Units (900–1700 IU) (reconstituted with 10 mL of sterile water).

- The actual strength will be printed on the vial label and on the box. Always check the actual dosage strength printed on the label to make sure you are using the strength prescribed by your healthcare provider.
- Always check the expiration date printed on the box.
- Do not use the product after the expiration date printed on the box.

How do I store VONVENDI?

- Store at refrigerated temperature 2°C to 8°C (36°F to 46°F) or room temperature not to exceed 30°C (86°F).
- Do not freeze.
- Store VONVENDI in the original box and protect from extreme exposure to light.
- Do not use beyond the expiration date.
- Do not use the product if the solution is not clear or if it contains particles after your draw it into the syringe.
- Use reconstituted product (after mixing dry product with supplied sterile water) immediately or within 3 hours of reconstitution.
- Store the reconstituted product at room temperature not to exceed 25°C (77°F) for up to 3 hours. Discard any unused reconstituted product after 3 hours.

What else should I know about VONVENDI and von Willebrand Disease?
Your body can form inhibitors to von Willebrand factor or factor VIII. An inhibitor is part of the body’s normal defense system. If you form inhibitors, they may stop VONVENDI or FVIII from working properly. Consult with your healthcare provider to make sure you are carefully monitored with blood tests for the development of inhibitors to von Willebrand factor or factor VIII.
Medicines are sometimes prescribed for purposes other than those listed here. Do not use VONVENDI for a condition for which it is not prescribed. Do not share VONVENDI with other people, even if they have the same symptoms that you have.

Resources at Takeda available to the patients:
For more product information on VONVENDI, please visit www.VONVENDI.com or call 1-877-TAKEDA-7 (1-877-825-3327).
For information on additional Takeda patient resources, please visit www.VONVENDI.com.
Manufactured by:
Takeda Pharmaceuticals U.S.A., Inc.
Cambridge, MA 02142U.S. License No. 1898
VONVENDI is a registered trademark of Baxalta Incorporated.
Takeda and are registered trademarks of Takeda Pharmaceutical Company Limited.
Mix2Vial® is a registered trademark of West Pharma. Services IL, Ltd., a subsidiary of West Pharmaceutical Services, Inc.
Patented: see www.takeda.com/en-us/patents
©2025 Takeda Pharmaceutical Company Limited. All rights reserved.
VON355

This Patient Information has been approved by the U.S. Food and Drug Administration. Revised: 9/2025

Instructions for Use
VONVENDI®
[von Willebrand factor (recombinant)] (For intravenous use only)

This Instructions for Use contains information on how to inject VONVENDI.

For first dose for each bleeding episode, use with recombinant factor VIII as instructed by your physician.

- Always follow the specific instructions given by your healthcare provider. The steps listed below are general guidelines for using VONVENDI. If you are unsure of the procedures, please call your healthcare provider before using.
- Call your healthcare provider right away if bleeding is not controlled after using VONVENDI.
- Your healthcare provider will prescribe the VONVENDI dose that you should take. If this is your first infusion to control a new bleeding episode, and if recombinant factor VIII in needed, be sure you also have the correct dose of recombinant factor VIII as instructed by your physician.
- Your healthcare provider may need to take blood tests from time to time.
- Talk to your healthcare provider before traveling. Plan to bring enough VONVENDI for your treatment during this time.
- Dispose of all materials, including any leftover reconstituted VONVENDI product, in an appropriate container.

See below for step-by-step instructions for reconstituting and administrating VONVENDI:

Reconstitution

1. Prepare a clean flat surface and gather all the materials you will need for the infusion. Check the expiration date, and let the VONVENDI warm up to room temperature. Wash your hands and put on clean exam gloves. If infusing yourself at home, the use of gloves is optional.
2. Remove the caps from the VONVENDI concentrate and diluent vials to expose the center of the rubber stoppers.

3. Disinfect each stopper with a separate sterile alcohol swab (or other suitable sterile solution suggested by your healthcare provider or hemophilia center) by rubbing the stopper for several seconds and allow it to dry prior to use. Place the vials on a flat surface.

4. Open the Mix2Vial device package by completely peeling away the lid, without touching the inside of the package. Do not remove the Mix2Vial device from the package.
5. Turn the package with the Mix2Vial device upside down and place it over the top of the diluent vial. Firmly insert the blue plastic spike of the device into the center of the diluent vial stopper by pushing straight down. Grip the package at its edge and lift it off the Mix2Vial device. Be careful not to touch the clear plastic spike. The diluent vial now has the Mix2Vial device connected to it and is ready to be connected to the VONVENDI vial.

6. To connect the diluent vial to the VONVENDI vial, turn the diluent vial over and place it on top of the vial containing VONVENDI concentrate. Fully insert the clear plastic spike into the VONVENDI vial stopper by firmly pushing straight down. This should be done right away to keep the liquid free of germs. The diluent will flow into the VONVENDI vial by vacuum. Verify that diluent transfer is complete. Do not use if vacuum has been lost.

7. Gently and continuously swirl the connected vials or allow the reconstituted product to sit for 5 minutes then gently swirl to ensure the powder is completely dissolved. Do not shake. Shaking will adversely affect the product. Do not refrigerate after reconstitution.
  Note: Some flakes or particles may remain in the reconstituted vial. The filter included in the Mix2Vial device will remove extraneous flakes or particles, and the resulting solution in the syringe should be clear and colorless. Do not use the solution in the syringe if it is cloudy or contains flakes or particles after filtration from the vial into the syringe.

8. Disconnect the two sides of the Mix2Vial from each other by holding the clear plastic side of the Mix2Vial device attached to the VONVENDI vial with one hand and the blue plastic side of the Mix2Vial device attached to the diluent vial with the other hand. Turn the blue plastic side counterclockwise and gently pull the two vials apart. Do not touch the end of the plastic connector attached to the VONVENDI vial containing the dissolved product. Place the VONVENDI vial on a flat work surface. Discard the empty diluent vial.

9. Draw air into the empty, sterile disposable plastic syringe by pulling back on the plunger. The amount of air should equal the amount of reconstituted VONVENDI that you will withdraw from the vial.

10. Leaving the VONVENDI vial (containing the dissolved product) on your flat work surface, connect the syringe to the clear plastic connector by attaching and turning the syringe clockwise (Figure A). Hold the vial with one hand and use the other hand to push the entire amount of air from the syringe into the vial (Figure B). The required amount of product will not be drawn into the syringe if all the air is not pushed into the vial.

Figure A

Figure B

11. Flip connected syringe and VONVENDI vial so the vial is on top. Be sure to keep the syringe plunger pressed in. Draw the VONVENDI into the syringe by pulling plunger back slowly. Do not push and pull solution back and forth between syringe and vial. Doing so may harm the integrity of the product. Inspect syringe visually for particulate matter; the solution should be clear and colorless in appearance. If flakes or particles are seen, do not use the solution and notify your healthcare provider.

12. When ready to infuse, disconnect the syringe by turning it counterclockwise.

13. If your dose requires more than one vial of VONVENDI, reconstitute each vial using a separate Mix2Vial device following the reconstitution steps above (2 to 8).
14. Up to two vials of VONVENDI may be pooled into a single syringe. If you have a second vial of reconstituted VONVENDI:
  a. Disconnect the syringe with reconstituted solution carefully from the first vial of VONVENDI by turning the syringe counterclockwise. Do not touch exposed connector.

  b. Pull the plunger back to draw air into the syringe containing the first vial of reconstituted VONVENDI. The amount of air added should equal the amount of reconstituted VONVENDI you will withdraw from the second vial. Do not touch exposed connector.

  c. Leave second vial of VONVENDI on flat surface and connect syringe by attaching to plastic connector and turning syringe clockwise.

  d. Flip connected syringe and second vial of VONVENDI so vial is on top (Figure C). Hold the vial with one hand and use the other hand to slowly push air into vial by pressing the syringe plunger (Figure D). Do not push any fluid from the syringe into the vial.

Figure C

Figure D

  e. Draw reconstituted VONVENDI from second vial of VONVENDI into syringe by slowly pulling back the plunger. Do not push any fluid from the syringe into the vial.

  f. Leave syringe attached to vial until ready to infuse to reduce risk of contamination. If your dose requires more than two vials of reconstituted VONVENDI, go back to Step 9 to draw your third vial into a NEW plastic syringe. No more than two vials of VONVENDI may be pooled into a single syringe. Pooling of more than two vials into a syringe may result in formation of filaments, which requires discarding of the solution in the syringe.

15. If you need to infuse recombinant factor VIII, reconstitute recombinant factor VIII as instructed in the package insert for that product. Do not administer your recombinant factor VIII until you have infused your complete dose of VONVENDI. Always follow your healthcare provider’s specific directions.

Administration

1. Attach the infusion needle to a syringe containing VONVENDI solution. For comfort, a winged (butterfly) infusion set is preferred. Point the needle up and remove any air bubbles by gently tapping the syringe with your finger and slowly and carefully pushing air out of the syringe and needle.
2. Apply a tourniquet and get the injection site ready by wiping the skin well with a sterile alcohol swab (or other suitable sterile solution suggested by your healthcare provider or hemophilia center).

3. Insert the needle into the vein and remove the tourniquet. Slowly infuse the VONVENDI. Do not infuse any faster than 4 mL per minute.
4. Disconnect the empty syringe. If your dose requires multiple syringes, attach and administer each additional syringe of VONVENDI one at a time.
5. Do not remove butterfly needle until all syringes have been infused and do not touch the Luer port that connects to the syringe.
6. If your healthcare provider has prescribed recombinant factor VIII, administer recombinant factor VIII within 10 minutes after you have infused your complete dose of VONVENDI.

7. Take the needle out of the vein and use sterile gauze to put pressure on the infusion site for several minutes.
8. Do not recap the needle. Place the needle, syringe, and empty VONVENDI and diluent vial(s) in a hard-walled sharps container for proper disposal. Do not dispose of these supplies in ordinary household trash.

Important: Contact your healthcare provider or local hemophilia treatment center if you experience any problems.

Manufactured by:
Takeda Pharmaceuticals U.S.A., Inc.
Cambridge, MA 02142
U.S. License No. 1898

VONVENDI is a registered trademark of Baxalta Incorporated.

Takeda and are registered trademarks of Takeda Pharmaceutical Company Limited.

Mix2Vial® is a registered trademark of West Pharma. Services IL, Ltd., a subsidiary of West Pharmaceutical Services, Inc.

Patented: see www.takeda.com/en-us/patents

©2025 Takeda Pharmaceutical Company Limited. All rights reserved.
VON355

This Instructions for Use has been approved by the U.S. Food and Drug Administration.
Revised: 9/2025

PRINCIPAL DISPLAY PANEL - Kit Carton - 650 IU

NDC 0944-7551-02

VONVENDI®
von Willebrand factor
(Recombinant)

ACTUAL POTENCY

Single-dose vials, lyophilized powder for solution

For Intravenous Administration After Reconstitution Only.

Rx Only

Takeda

PRINCIPAL DISPLAY PANEL - 650 IU Vial Label

NDC 0944-7550-01

VONVENDI®
von Willebrand factor
(Recombinant)

Single-dose vial, lyophilized powder, sterile

Rx Only

For Intravenous Administration After
Reconstitution Only.

Takeda Pharmaceuticals U.S.A., Inc.
Cambridge, MA 02142
U.S. License No. 1898

PRINCIPAL DISPLAY PANEL - Kit Carton - 1300 IU

NDC 0944-7553-02

VONVENDI®
von Willebrand factor
(Recombinant)

ACTUAL POTENCY

Single-dose vials, lyophilized powder for solution

For Intravenous Administration After Reconstitution Only.

Rx Only

Takeda

PRINCIPAL DISPLAY PANEL - 1300 IU Vial Label

NDC 0944-7552-01

VONVENDI®
von Willebrand factor
(Recombinant)

Single-dose vial, lyophilized powder, sterile

Rx Only

For Intravenous Administration After
Reconstitution Only.

Takeda Pharmaceuticals U.S.A., Inc.
Cambridge, MA 02142
U.S. License No. 1898